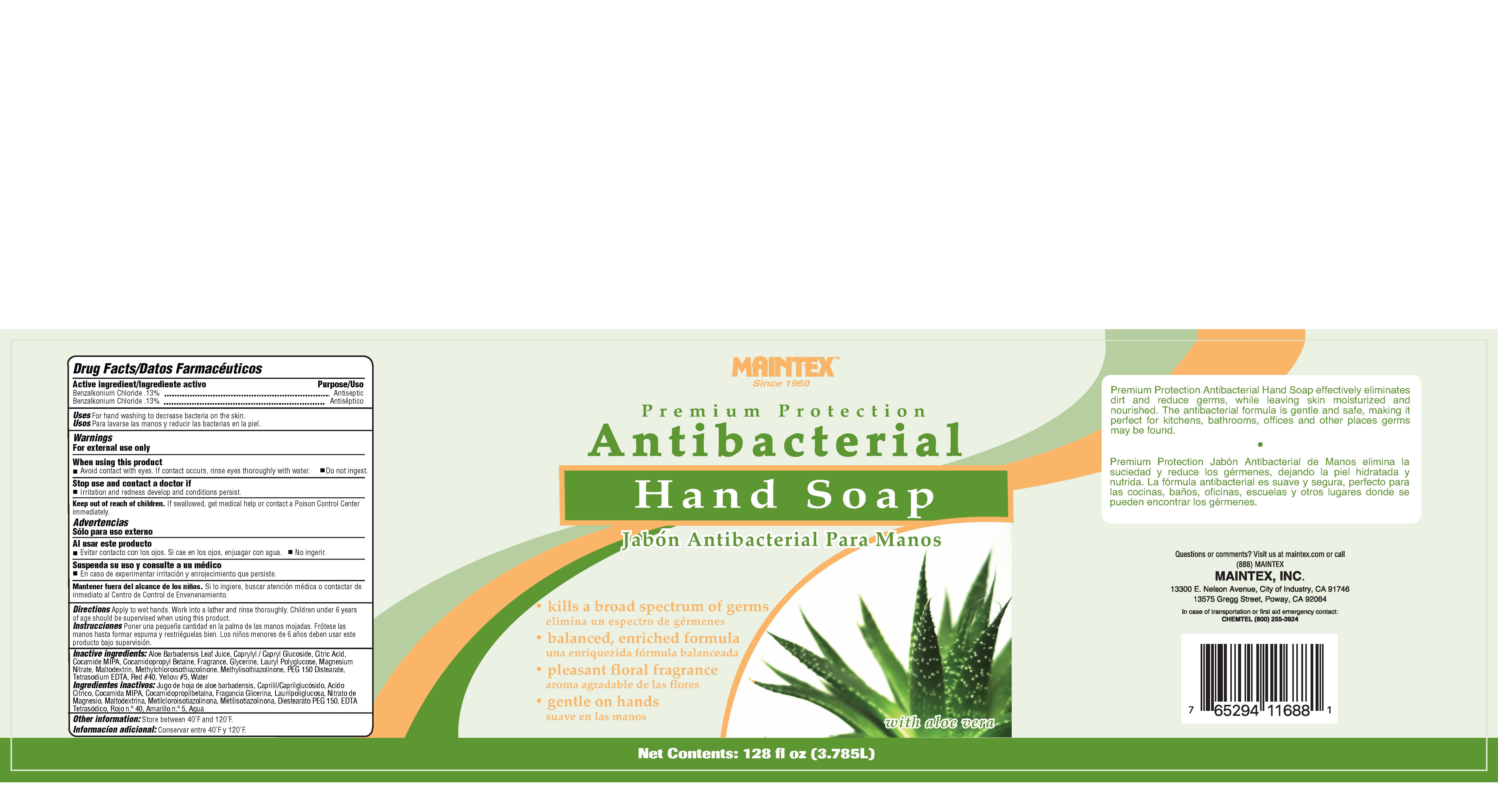 DRUG LABEL: Premium Protection Antibacterial Hand
NDC: 77617-002 | Form: LIQUID
Manufacturer: Maintex
Category: otc | Type: HUMAN OTC DRUG LABEL
Date: 20251106

ACTIVE INGREDIENTS: BENZALKONIUM CHLORIDE 13 kg/100 kg
INACTIVE INGREDIENTS: ALOE VERA FLOWER; CAPRYLYL/CAPRYL OLIGOGLUCOSIDE; ANHYDROUS CITRIC ACID; COCO MONOISOPROPANOLAMIDE; COCAMIDOPROPYL BETAINE; GLYCERIN; LAURYL GLUCOSIDE; MAGNESIUM NITRATE; MALTODEXTRIN; METHYLCHLOROISOTHIAZOLINONE; METHYLISOTHIAZOLINONE; PEG-150 DISTEARATE; FD&C RED NO. 40; EDETATE SODIUM; WATER; FD&C YELLOW NO. 5

Premium Protection Antibacterial Hand Soap

ACTIVE INGREDIENT

Benzalkonium Chloride......0.13%

Purpose

Antiseptic

Uses

For hand washing to decrease bacteria on the skin.

Warnings

For external use only.

When Using this Product

Avoid contact with the eyes.

In case of eye contact, rinse eyes thoroughly with water.

Do not ingest.

Stop use and contact a doctor if irritation and redness develop

and conditions persist.

Keep out of reach of children.

If swallowed, get medical help

or contact Posion Control Center immediately

Directions

Apply to wet hands. Work into a latther and rinse thoroughly. Children under 6 years of age should be supervised when using this product.

Inactive Ingredients

Water, Cocamidopropyl Betaine, PEG 150 Distearate, Caprylyl Glucoside, Glycerine, Cocamide MIPA, Tetrasodium EDTA, Fragrance, Citric Acid, Aloe Vera, Benzisothiazol, Methylisothiozol, Yellow #5, Red #40